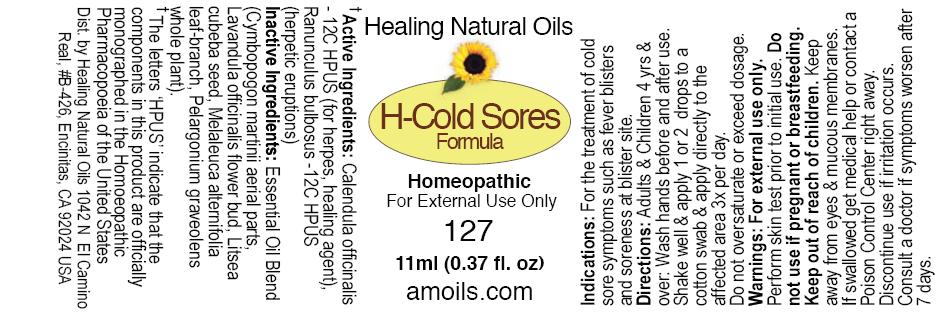 DRUG LABEL: H-Cold Sores Formula
NDC: 61077-127 | Form: OIL
Manufacturer: Healing Natural Oils LLC
Category: homeopathic | Type: HUMAN OTC DRUG LABEL
Date: 20241211

ACTIVE INGREDIENTS: CALENDULA OFFICINALIS FLOWERING TOP 12 [hp_C]/11 mL; RANUNCULUS BULBOSUS 12 [hp_C]/11 mL
INACTIVE INGREDIENTS: CYMBOPOGON MARTINI TOP; LAVANDULA ANGUSTIFOLIA FLOWER; LITSEA CUBEBA FRUIT; MELALEUCA ALTERNIFOLIA LEAF; PELARGONIUM GRAVEOLENS WHOLE

Active Ingredients:

Calendula officinalis -12C HPUS,

Ranunculus bulbosus- 12C HPUS

Purpose

Calendula officinalis -12C HPUS (for herpes, healing agent),
Ranunculus bulbosus -12C HPUS (herpetic eruptions)
The letters ‘HPUS’ indicate that the components in this product are officially
monographed in the Homoeopathic Pharmacopoeia of the United States

Inactive Ingredients:

Essential Oil Blend (Cymbopogon martinii aerial parts,
Lavandula officinalis flower bud, Litsea cubeba seed,
Melaleuca alternifolia leaf-branch, Pelargonium graveolens whole
plant)

Indications:

For the treatment of cold sore symptoms, such as fever blisters, soreness at blister site.

Directions:

Adults and Children 4 yrs and over: Wash hands before and after use.
Shake well and apply 1 or 2 drops to a cotton swab and apply directly to the affected area 3x per day.
Do not oversaturate or exceed dosage.

Warnings:

For external use only.

Perform skin test prior to initial use.

Do not use if pregnant or breastfeeding.

Keep out of reach of children.

OTHER SAFETY INFORMATION

Keep away from eyes and mucous membranes. If swallowed get medical help
or contact a Poison Control Center right away.

Discontinue use if irritation occurs.

ASK DOCTOR

Consult a doctor if symptoms worsen after 7 days.

DESCRIPTION

Dist. by Healing Natural Oils 1042 N El Camino Real,

#B-426, Encinitas, CA 92024 USA

Principal Display Panel

Healing Natural Oils

H-Cold Sores
Formula

Homeopathic

For External Use Only

127

11ml (0.37 fl. oz)
amoils.com